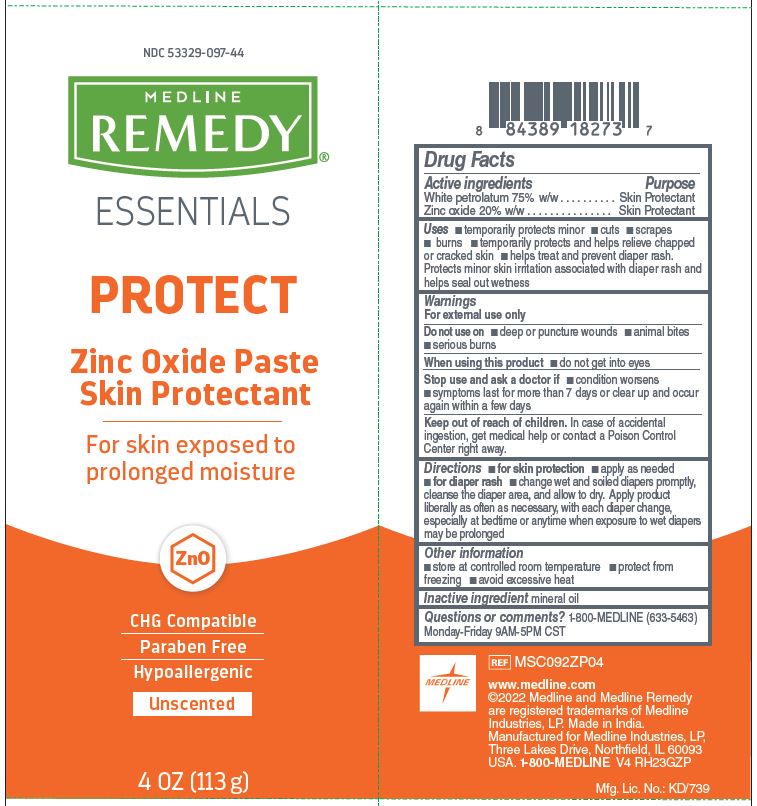 DRUG LABEL: Remedy Essentials
NDC: 53329-097 | Form: PASTE
Manufacturer: Medline Industries, LP
Category: otc | Type: HUMAN OTC DRUG LABEL
Date: 20260105

ACTIVE INGREDIENTS: ZINC OXIDE 20 g/100 g; PETROLATUM 75 g/100 g
INACTIVE INGREDIENTS: MINERAL OIL

097 Medline Remedy Essentials Zinc Protectant Paste

Active ingredient

White Petrolatum 75%

Zinc Oxide 20%

Purpose

Skin Protectant

Uses

- temporarily protects minor cuts, scrapes, and burns
- temporarily protects and helps relieve chapped or cracked skin
- helps treat and prevent diaper rash. Protects minor skin irritation associated with diaper rash and helps seal out wetness

Warnings

For external use only.

Do not use on

- deep or puncture wounds
- animal bites
- serious burns

When using this product

- do not get into eyes

Stop use and ask a doctor if

- condition worsens
- symptoms last for more than 7 days or clear up and occur again within a few days

Keep out of reach of children.

If swallowed, get medical help or contact a Poison Control Center right away.

Directions

- for skin protection: apply as needed
- for diaper rash: change wet and soiled diapers promptly, cleanse the diaper area, and allow to dry. Apply product liberally as often as necessary, with each diaper change, especially at bedtime or anytime when exposure to wet diapers may be prolonged

Other information

- store at controlled room temperature
- protect from freezing
- avoid excessive heat

Inactive ingredients

mineral oil

Manufacturing Information

Manufactured for Medline Industries, LP

Three Lakes Drive, Northfield, IL 60093 USA

Made in India

www.medline.com

1-800-MEDLINE

REF: MSC092ZP04

V4 RH23GZP